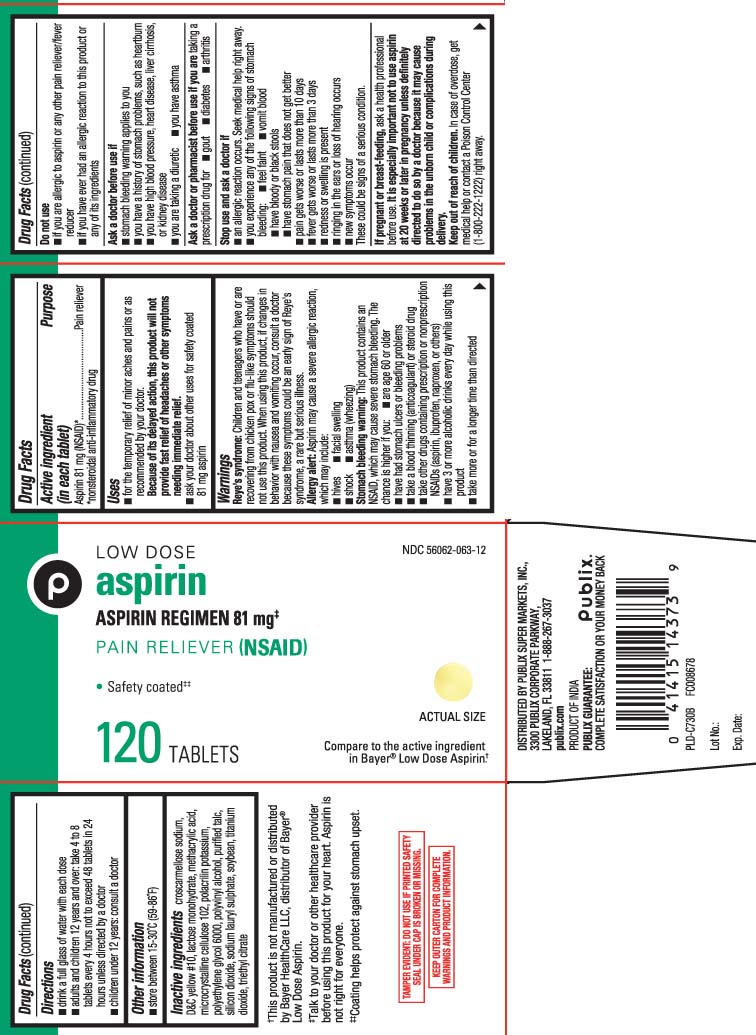 DRUG LABEL: Aspirin
NDC: 56062-063 | Form: TABLET
Manufacturer: Publix Supermarkets, Inc.
Category: otc | Type: HUMAN OTC DRUG LABEL
Date: 20241101

ACTIVE INGREDIENTS: ASPIRIN 81 mg/1 1
INACTIVE INGREDIENTS: CROSCARMELLOSE SODIUM; D&C YELLOW NO. 10; LACTOSE MONOHYDRATE; METHACRYLIC ACID; MICROCRYSTALLINE CELLULOSE 102; POLACRILIN POTASSIUM; POLYVINYL ALCOHOL, UNSPECIFIED; POLYETHYLENE GLYCOL 6000; TALC; SILICON DIOXIDE; SODIUM LAURYL SULFATE; SOYBEAN; TITANIUM DIOXIDE; TRIETHYL CITRATE

Aspirin 81mg Enteric Coated TCB

Active ingredient(in each tablet)

Aspirin 81 mg (NSAID)*

*nonsteroidal anti-inflammatory drug

Purpose

Pain reliever

Uses

- for the temporary relief of minor aches and pains or as recommended by a doctor.
  Because of its delayed action, this product will not provide fast relief of headaches or other symptoms needing immediate relief.
- ask your doctor about other uses for safety coated 81 mg aspirin

Warnings

Reye's syndrome: Children and teenagers who have or are recovering from chicken pox or flu-like symptoms should not use this product. When using this product, if changes in behavior with nausea and vomiting occur, consult a doctor because these symptoms could be an early sign of Reye's syndrome, a rare but serious illness.

Allergy alert: Aspirin may cause a severs allergic reaction, which may include:

- hives
- shock
- facial swelling
- asthma (wheezing)

Stomach bleeding warning: This product contains an NSAID, which may cause severe stomach bleeding. The chance is higher if you

- are age 60 or older
- have had stomach ulcers or bleeding problems
- take a blood thinning (anticoagulant) or steroid drug
- take other drugs containing prescription or nonprescription NSAIDs (aspirin, ibuprofen, naproxen, or others)
- have 3 or more alcoholic drinks every day while using this product
- take more or for longer time than directed

Do not use

- if you are allergic to aspirin or any other pain reliever/fever reducer
- if you have ever had an allergic reaction to this product or any of its ingredients

Ask a doctor before use if

- stomach bleeding warning applies to you
- you have history of stomach problems, such as heartburn
- you have high blood pressure, heart disease, liver cirrhosis, or kidney disease
- you are taking a diuretic
- you have asthma

Ask a doctor or pharmacist before use if you are

taking a prescription drug for

- gout
- diabetes
- arthritis

Stop use and ask a doctor if

- an allergic reaction occurs. Seek medical help right away.
- you experience any of the following signs of stomach bleeding
  - feel faint
  - vomit blood
  - have bloody or black stools
  - have stomach pain that does not get better
- pain gets worse or lasts more than 10 days
- fever gets worse or lasts more than 3 days
- redness or swelling is present
- ringing in the ears or loss of hearing occurs
- new symptoms occur

These could be a signs of a serious condition.

Pregnancy/Breast-feeding,

ask a health professional before use. It is especially important not to use aspirin at 20 weeks or later in pregnancy unless definitely directed to do so by a doctor because it may cause problems in the unborn child or complications during delivery.

Keep out of reach of children.

In case of overdose, get medical help pr contact a Poison Control Center (1-800-222-1222) right away.

Directions

- drink a full glass of water each dose
- adults and children 12 years and over: take 4 to 8 tablets every 4 hours not to exceed 48 tablets in 24 hours unless directed by a doctor
- children under 12 years: consult a doctor

Other information

- store between 15-30ºC (59-86ºF)

Inactive ingredients

Croscarmellose sodium, D&C yellow #10, lactose monohydrate, methacrylic acid, microcrystalline cellulose 102, polacrilin potassium, polyethylene glycol 6000, polyvinyl alcohol, purfied talc, silicon dioxide, sodium lauryl sulphate, soybean, titanium dioxide, triethyl citrate

Principal Display Panel

Compare to the active ingredient in Bayer® Low Dose Aspirin†

LOW DOSE

aspirin

ASPIRIN REGIMEN 81 mg±

PAIN RELIEVER (NSAID)

- Safety coated±±

TABLETS

†This product is not manufactured or distributed by Bayer HealthCare LLC, distributor of Bayer® Low Dose Aspirin.

±Talk to your doctor or other healthcare provider before using this product for your hearth. Aspirin is not right for everyone.

±±Coating helps protect against stomach upset.

TAMPER EVIDENT: DO NOR USE IF PRINTED SAFETY SEAL UNDER CAP IS BROKEN OR MISSING

KEEP OUTER CARTON FOR COMPLETE WARNINGS AND PRODUCT INFORMATION.

DISTRIBUTED BY PUBLIX SUPERMARKETS, INC.,

3300 PUBLIX CORPORATE PARKWAY,

LAKELAND, FL 33811

Package label

PUBLIX Low Dose Aspirin